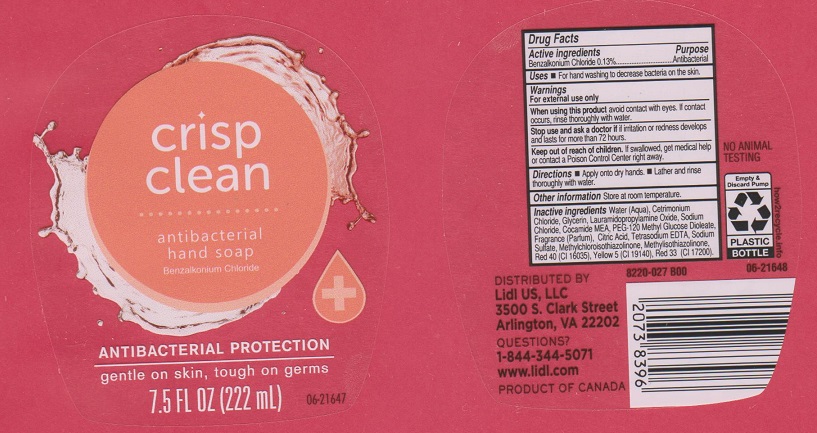 DRUG LABEL: Crisp Clean Antibacterial Hand
NDC: 63148-109 | Form: SOAP
Manufacturer: Apollo Health and Beauty Care Inc.
Category: otc | Type: HUMAN OTC DRUG LABEL
Date: 20170330

ACTIVE INGREDIENTS: BENZALKONIUM CHLORIDE 1.3 mg/1 mL
INACTIVE INGREDIENTS: WATER; CETRIMONIUM CHLORIDE; GLYCERIN; LAURAMIDOPROPYLAMINE OXIDE; SODIUM CHLORIDE; COCO MONOETHANOLAMIDE; PEG-120 METHYL GLUCOSE DIOLEATE; CITRIC ACID MONOHYDRATE; EDETATE SODIUM; SODIUM SULFATE; METHYLCHLOROISOTHIAZOLINONE; METHYLISOTHIAZOLINONE; FD&C RED NO. 40; FD&C YELLOW NO. 5; D&C RED NO. 33

Drug Facts

Active ingredients

Benzalkonium Chloride 0.13%

Purpose

Antibacterial

Uses

For hand washing to decrease bacteria on the skin.

Warnings

For external use only.

When using this product

avoid contact with eyes. If contact occurs, rinse thoroughly with water.

Stop use and ask a doctor

if irritation or redness develops and lasts for more than 72 hours.

Keep out of reach of children.

If swallowed, get medical help or contact a Poison Control Center right away.

Directions

- Apply onto dry hands.
- Lather and rinse thoroughly with water.

Other information

Store at room temperature.

Inactive ingredients

Water (Aqua), Cetrimonium Chloride, Glycerin, Lauramidopropylamine Oxide, Sodium Chloride, Cocamide MEA, PEG-120 Methyl Glucose Dioleate, Fragrance (Parfum), Citric Acid, Tetrasodium EDTA, Sodium Sulfate, Methylchloroisothiazolinone, Methylisothiazolinone, Red 40 (CI 16035), Yellow 5 (CI 19140), Red 33 (CI 17200).